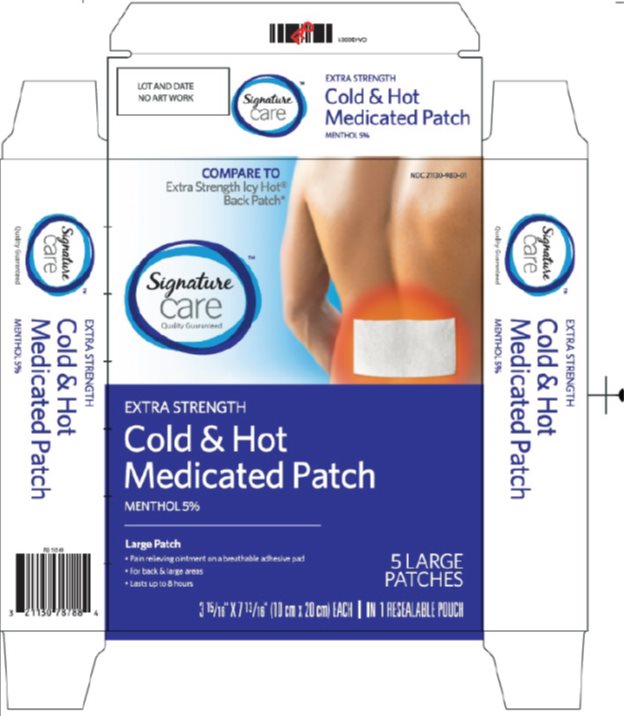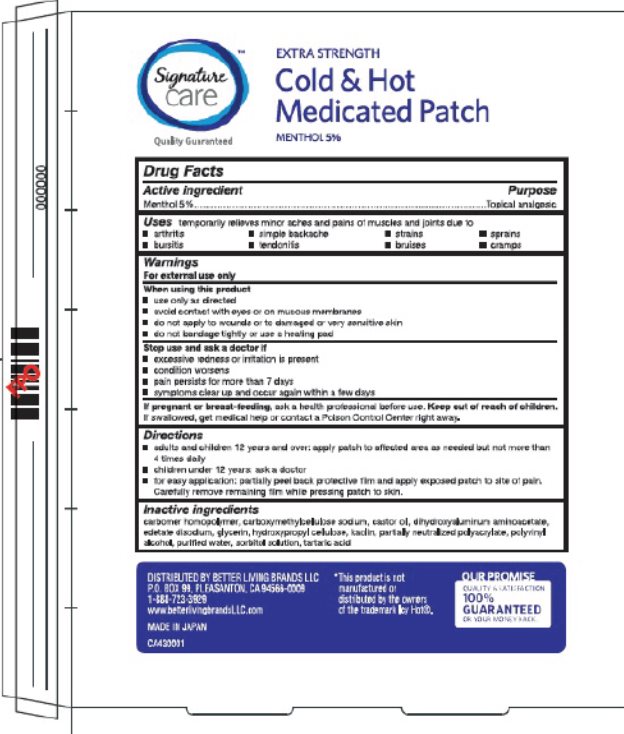 DRUG LABEL: Signature Care Cold and Hot Medicated
NDC: 21130-980 | Form: PATCH
Manufacturer: Safeway
Category: otc | Type: HUMAN OTC DRUG LABEL
Date: 20241217

ACTIVE INGREDIENTS: MENTHOL, UNSPECIFIED FORM 50 mg/1 1
INACTIVE INGREDIENTS: CARBOMER HOMOPOLYMER TYPE B (ALLYL PENTAERYTHRITOL CROSSLINKED); CARBOXYMETHYLCELLULOSE SODIUM, UNSPECIFIED FORM; CASTOR OIL; DIHYDROXYALUMINUM AMINOACETATE; EDETATE DISODIUM; GLYCERIN; HYDROXYPROPYL CELLULOSE, UNSPECIFIED; KAOLIN; POLYVINYL ALCOHOL, UNSPECIFIED; POLYACRYLIC ACID (250000 MW); WATER; SORBITOL; TARTARIC ACID

Drug Facts - Signature Care Cold and Hot Medicated

Active ingredient

Menthol 5%

Purpose

Menthol - Topical analgesic

Uses

temporarily relieves minor aches and pains of muscles and joints due to

- arthritis
- simple backache
- strains
- sprains
- bursitis
- tendonitis
- bruises
- cramps

Warnings

For external use only

When using this product

- use only as directed
- avoid contact with eyes or on mucous membranes
- do not apply to wounds or to damaged or very sensitive skin
- do not bandage tightly or use with a heating pad

Stop use and ask a doctor if

- excessive redness or irritation is present
- condition worsens
- pain persist for more than 7 days
- symptoms clear up and occur again within a few days

If pregnant or breast-feeding,

ask a health professional before use.

Keep out of reach of children.

If swallowed, get medical help or contact a Poison Control Center right away.

Directions

- adults and children 12 years and over: apply patch to affected area as needed but not more than 4 times daily
- children under 12 years: ask a doctor
- for easy application; partially peel back protective film and apply exposed patch to site of pain. Carefully remove remaining film while pressing patch to skin.

Inactive ingredients

carbomer homopolymer, carboxymethylcellulose sodium, castor oil, dihydroxyaluminum aminoacetate, edetate disodium, glycerin, hydroxypropyl cellulose, kaolin, partially neutralized polyacrylate, polyvinyl alcohol, purified water, sorbitol solution, tartaric acid